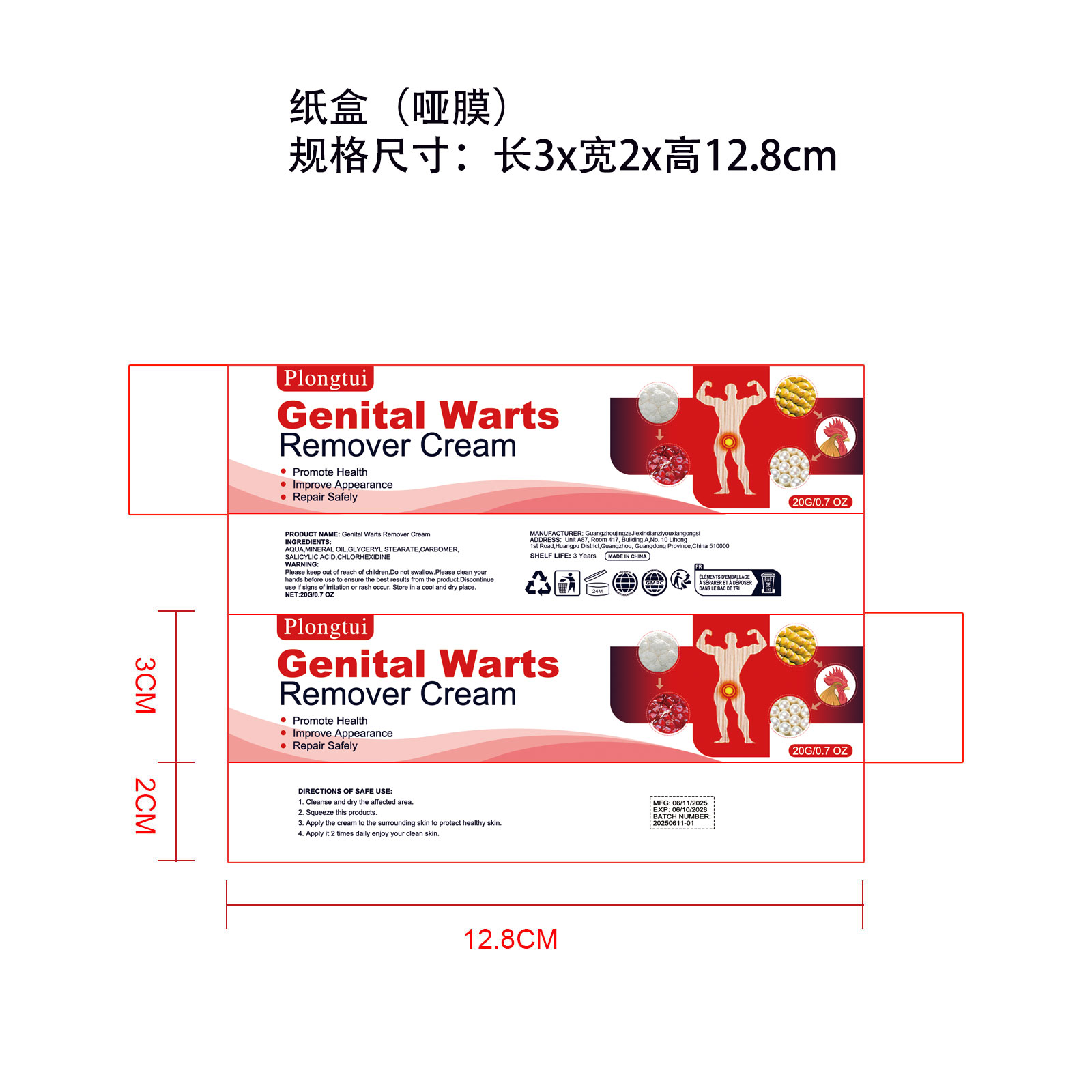 DRUG LABEL: Plongtui Genital Warts Remover
NDC: 85922-369 | Form: CREAM
Manufacturer: Guangzhou Jingze Jiexin Electronics Co Ltd
Category: homeopathic | Type: HUMAN OTC DRUG LABEL
Date: 20250708

ACTIVE INGREDIENTS: CHLORHEXIDINE 1 g/1 1; SALICYLIC ACID 1 g/1 1
INACTIVE INGREDIENTS: GLYCERYL STEARATE; CARBOMER; AQUA; MINERAL OIL

Keep out of reach of children section

PURPOSE

Genital Warts Remover

ACTIVE INGREDIENT

SALICYLIC ACID,CHLORHEXIDINE

Keep out of reach of children

DOSAGE AND ADMINISTRATION

20G/0.7 OZ

INACTIVE INGREDIENT

AQUA,MINERAL OIL,GLYCERYL STEARATE,CARBOMER

INDICATIONS AND USAGE

Genital Warts Remover